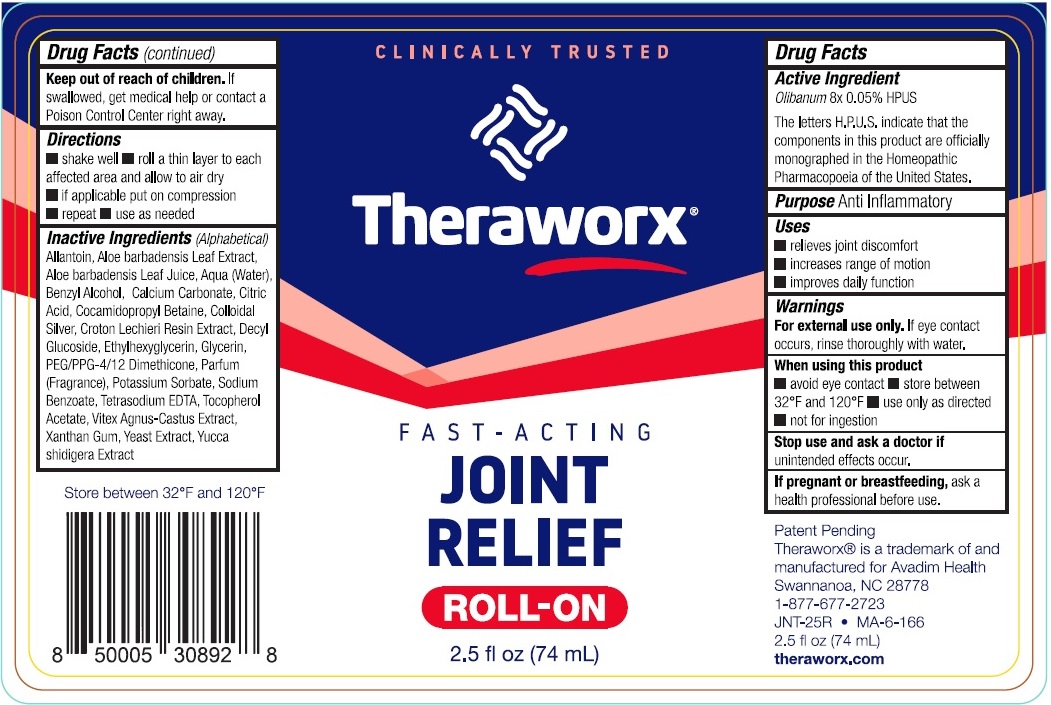 DRUG LABEL: Theraworx Joint Relief Roll On
NDC: 61594-027 | Form: LIQUID
Manufacturer: AVADIM HOLDINGS, INC.
Category: homeopathic | Type: HUMAN OTC DRUG LABEL
Date: 20230831

ACTIVE INGREDIENTS: FRANKINCENSE 8 [hp_X]/1 mL
INACTIVE INGREDIENTS: ALLANTOIN; ALOE VERA LEAF; WATER; BENZYL ALCOHOL; CALCIUM CARBONATE; CITRIC ACID MONOHYDRATE; COCAMIDOPROPYL BETAINE; SILVER; CROTON LECHLERI RESIN; DECYL GLUCOSIDE; ETHYLHEXYLGLYCERIN; GLYCERIN; PEG/PPG-4/12 DIMETHICONE; POTASSIUM SORBATE; SODIUM BENZOATE; EDETATE SODIUM; .ALPHA.-TOCOPHEROL ACETATE; CHASTE TREE FRUIT; XANTHAN GUM; YEAST, UNSPECIFIED; YUCCA SCHIDIGERA WHOLE

Theraworx Joint Relief Roll On

Active Ingredient

Olibanum 8X 0.05% HPUS

The letters H.P.U.S. indicate that the components in this product are officially monographed in the homeopathic pharmacopoeia of the United State.

Purpose

Anti Inflammatory

Uses

- relieves joint discomfort
- increase range of motion
- improves daily function

Warnings

For external use only.If eye contact occurs, rinse thoroughly with water.

When using this product

- avoid eye contact
- store between 32°F and 120°F
- use only as directed
- not for ingestion

Stop use and ask a doctor if

unintended effects occur.

If pregnant or breastfeeding,

ask a health professional before use.

Keep out of reach of children.

If swallowed, get medical help or contact a Poison Control Center right away.

Directions

- shake well
- roll a thin layer to each affected area and allow to air dry
- if applicable put on compression
- repeat
- use as needed

Inactive Ingredients (Alphabetical)

Allantoin, Aloe barbadensis Leaf Extract, Aloe barbadensis Leaf Juice, Aqua (Water), Benzyl Alcohol, Calcium Carbonate, Citric Acid, Cocamidopropyl Betaine, Colloidal Silver, Croton Lechieri Resin Extract, Decyl Glucoside, Ethylhexylglycerin, Glycerin, PEG/PPG-4/12 Dimethicone, Parfum (Fragrance), Potassium Sorbate, Sodium Benzoate, Tetrasodium EDTA, Tocopherol Acetate, Vitex Agnus- Castus Extract, Xanthan Gum, Yeast Extract, Yucca shidigera Extract